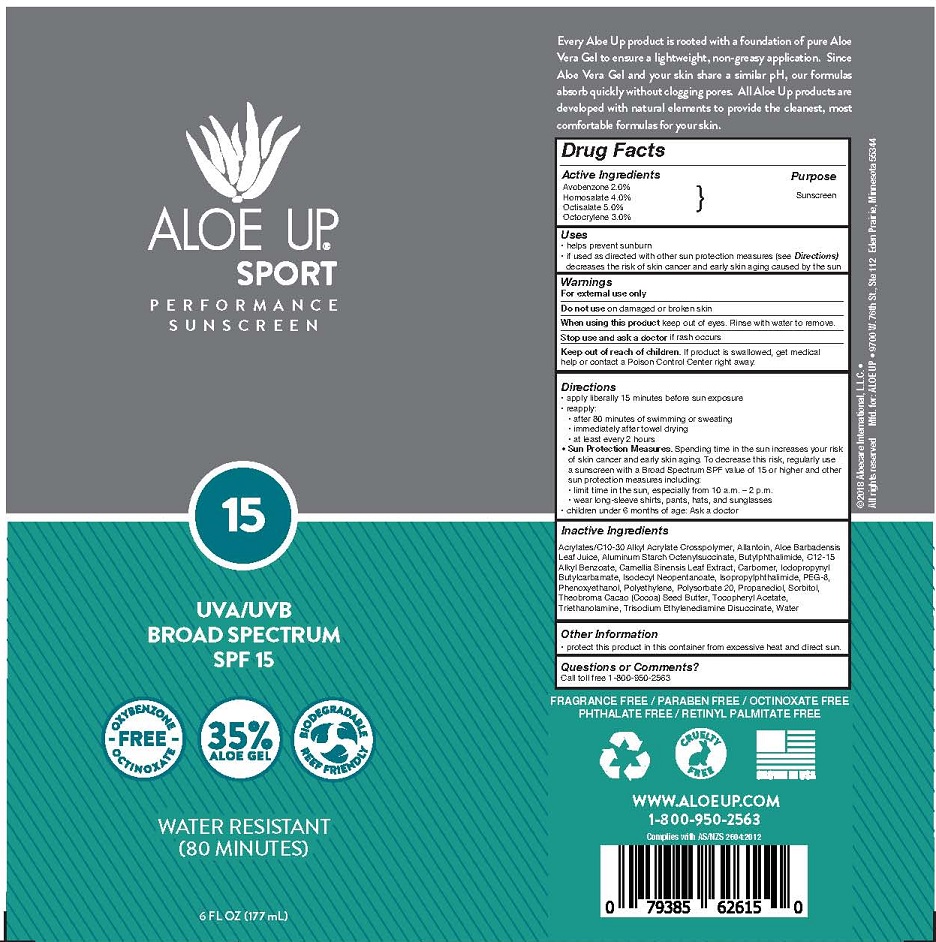 DRUG LABEL: ALOE UP SPORT
NDC: 61477-217 | Form: LOTION
Manufacturer: Aloe Care International, LLC
Category: otc | Type: HUMAN OTC DRUG LABEL
Date: 20260128

ACTIVE INGREDIENTS: AVOBENZONE 2 g/100 mL; HOMOSALATE 4 g/100 mL; OCTISALATE 5 g/100 mL; OCTOCRYLENE 3 g/100 mL
INACTIVE INGREDIENTS: CARBOMER INTERPOLYMER TYPE A (55000 CPS); ALLANTOIN; ALOE BARBADENSIS LEAF JUICE; ALUMINUM STARCH OCTENYLSUCCINATE; 3-BUTYLPHTHALIDE; ALKYL (C12-15) BENZOATE; CAMELLIA SINENSIS WHOLE; ETHYLHEXYLGLYCERIN; ISODECYL NEOPENTANOATE; ISOPROPYLPHTHALIMIDE; POLYETHYLENE; PHENOXYETHANOL; PEG-8; POLYSORBATE 20; PROPANEDIOL; SORBITOL; COCOA BUTTER; .ALPHA.-TOCOPHEROL ACETATE; SODIUM HYDROXIDE; TRISODIUM ETHYLENEDIAMINE DISUCCINATE; WATER

ALOE UP - SPORT SPF 15 LOTION (61477-217)

ACTIVE INGREDIENTS

AVOBENZONE (2.0%)

HOMOSALATE (4.0%)

OCTISALATE (5.0%)

OCTOCRYLENE (3.0%)

PURPOSE

SUNSCREEN

INDICATIONS

- HELPS PREVENT SUNBURN
- if used as directed with other sun protection measures (see Directions) decreases the risk of skin cancer and early skin aging caused by the sun

DIRECTIONS

• apply liberally 15 minutes before sun exposure
• reapply:
• after 80 minutes of swimming or sweating
• immediately after towel drying
• at least every 2 hours
• Sun Protection Measures. Spending time in the sun increases your risk of skin cancer and early skin aging. To decrease this risk, regularly use a sunscreen with a Broad Spectrum SPF value of 15 or higher and other sun protection measures including:
• limit time in the sun, especially from 10 a.m. – 2 p.m.
• wear long-sleeve shirts, pants, hats, and sunglasses
• children under 6 months of age: Ask a doctor

Keep out of reach of children. If product is swallowed, get medical help or contact a Poison Control Center right away.

WARNINGS

For external use only

Do not use on damaged or broken skin

When using this product keep out of eyes. Rinse with water to remove.

Stop use and ask a doctor if rash occurs

INACTIVE INGREDIENTS

Acrylates/C10-30 Alkyl Acrylate Crosspolymer, Allantoin, Aloe Barbadensis Leaf Juice, Aluminum Starch Octenylsuccinate, Butylphthalimide, C12-15 Alkyl Benzoate, Camellia Sinensis Leaf Extract, Carbomer, Iodopropynyl Butylcarbamate, Isodecyl Neopentanoate, Isopropylphthalimide, PEG-8, Phenoxyethanol, Polyethylene, Polysorbate 20, Propanediol, Sorbitol,
Theobroma Cacao (Cocoa) Seed Butter, Tocopheryl Acetate, Triethanolamine, Trisodium Ethylenediamine Disuccinate, Water

OTHER INFORMATION

- protect this product in this container from excessive heat and direct sun.

QUESTIONS OR COMMENTS?

Call toll free 1-800-950-2563